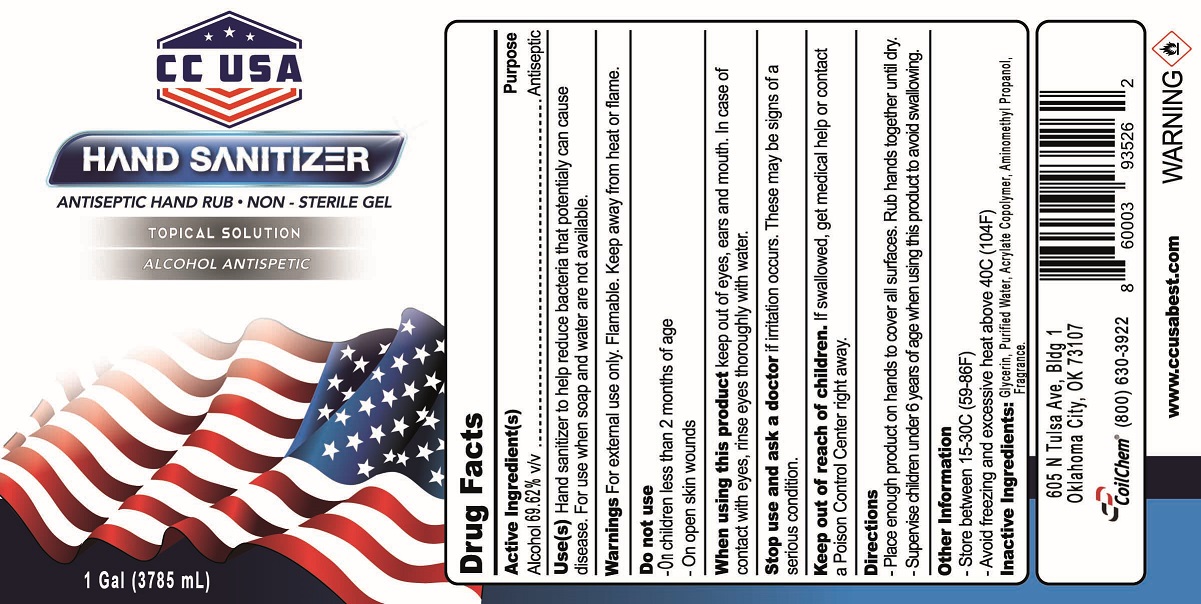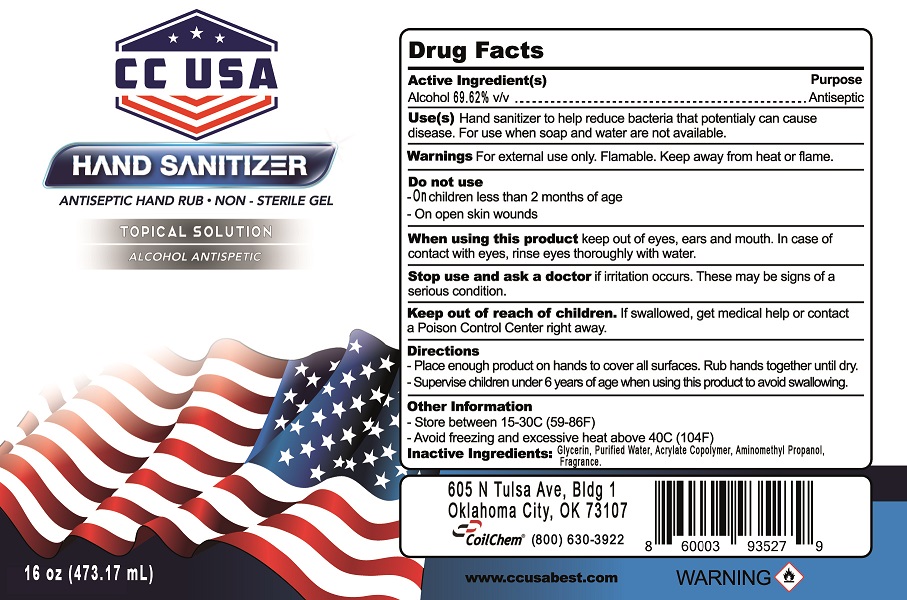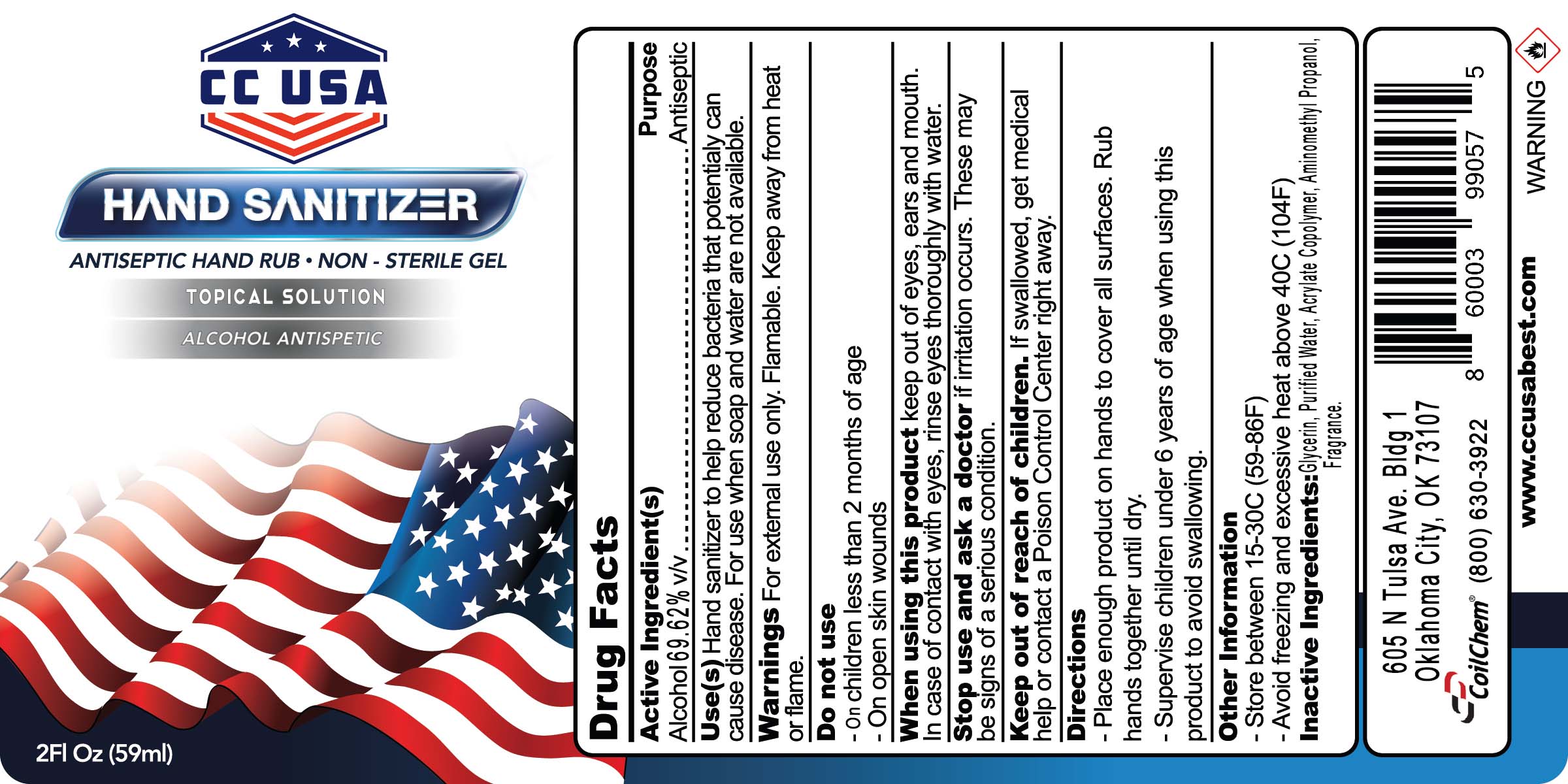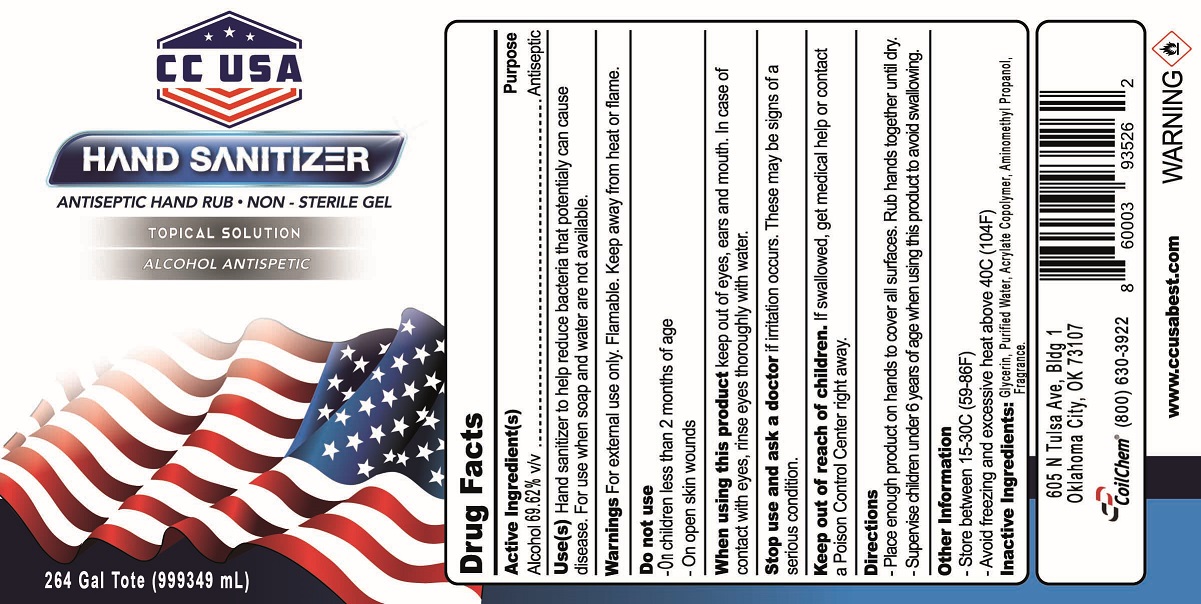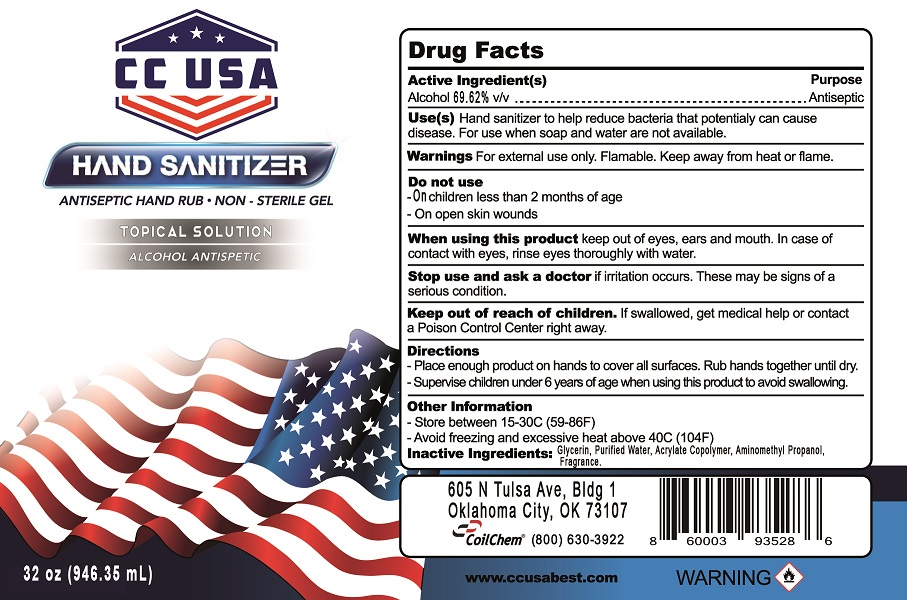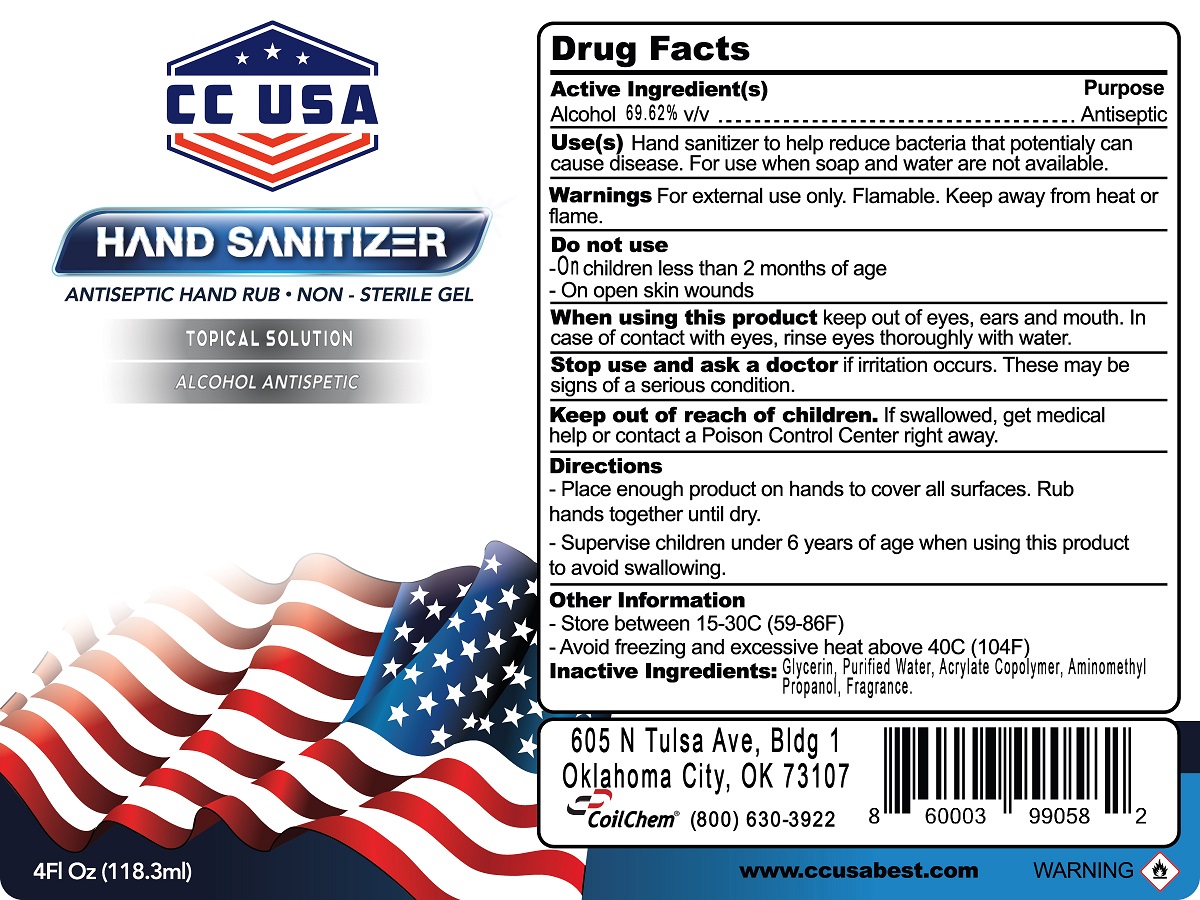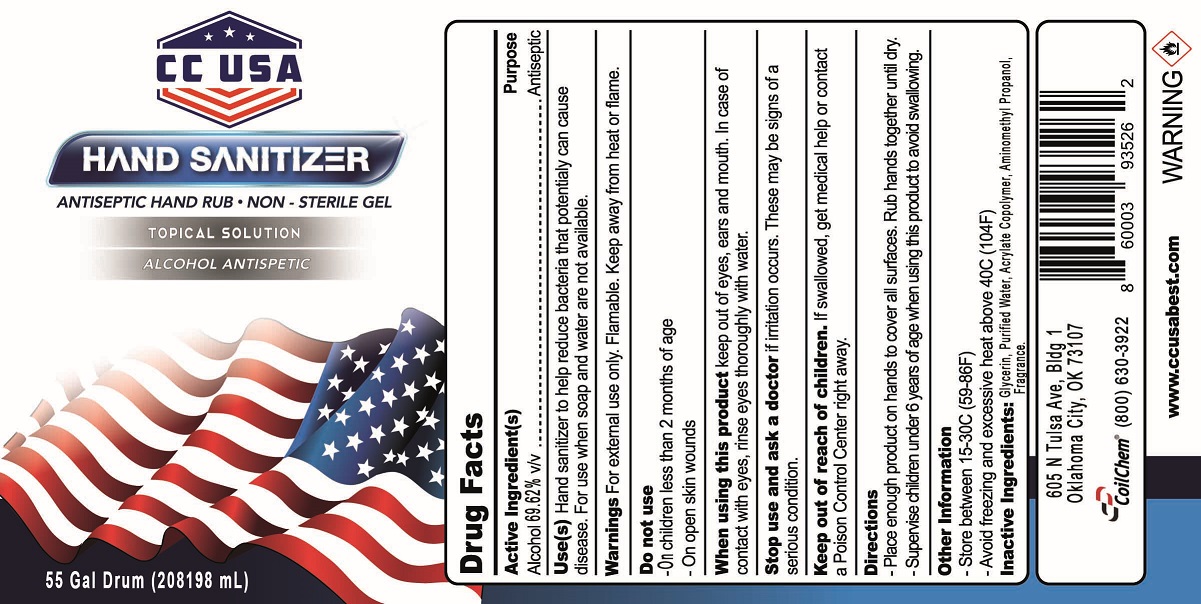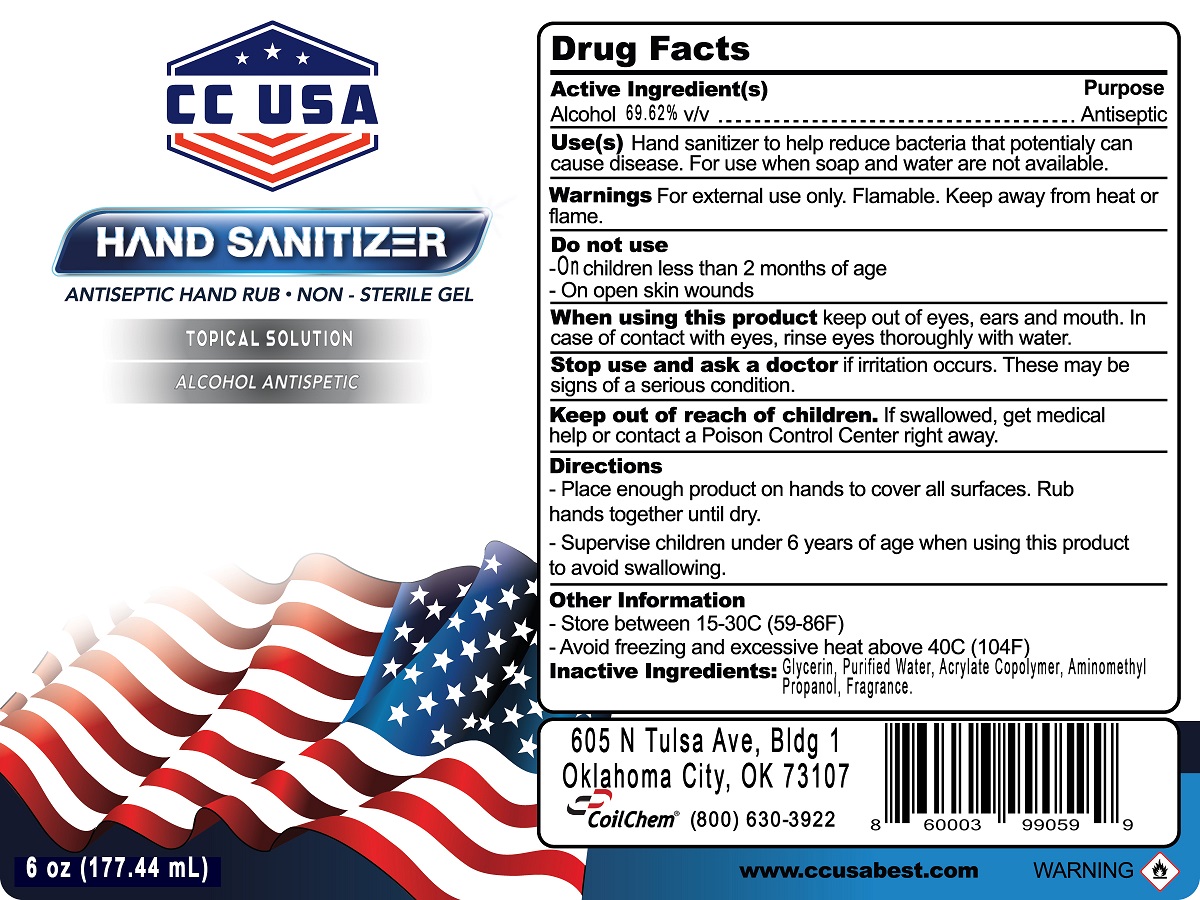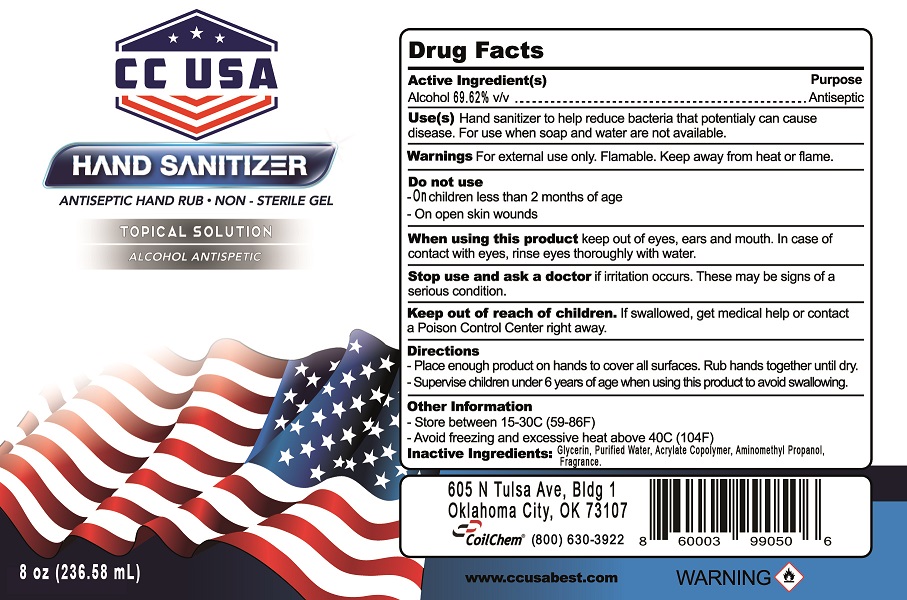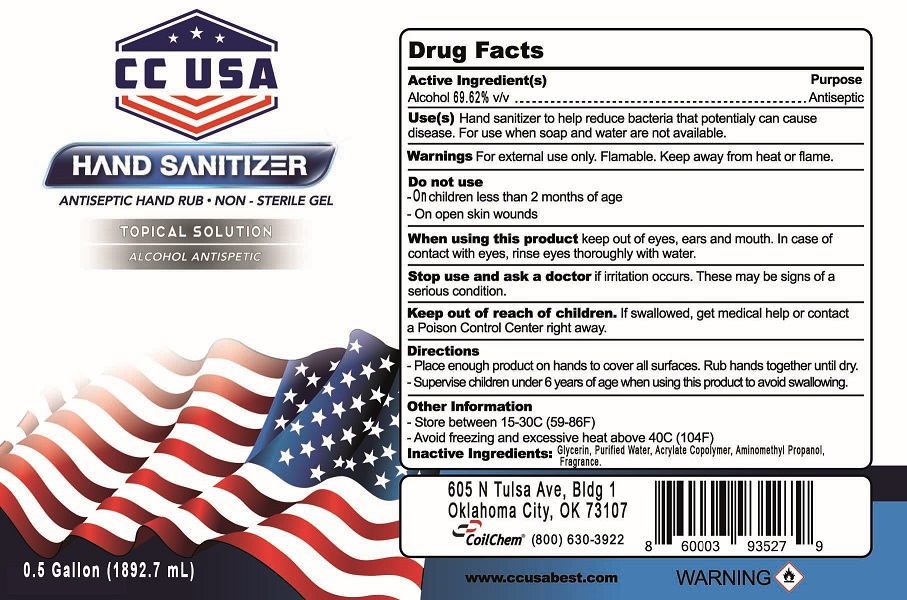 DRUG LABEL: CC USA Best Gel Hand Sanitizer
NDC: 75508-004 | Form: GEL
Manufacturer: Coil Chem LLC
Category: otc | Type: HUMAN OTC DRUG LABEL
Date: 20200831

ACTIVE INGREDIENTS: ALCOHOL 69.62 mL/100 mL
INACTIVE INGREDIENTS: GLYCERIN 1.17 mL/100 mL; AMINOMETHYL PROPANEDIOL 0.18 mL/100 mL; METHACRYLIC ACID - ETHYL ACRYLATE COPOLYMER (4500 MPA.S) 4.08 mL/100 mL; FRAGRANCE CLEAN ORC0600327 0.24 mL/100 mL; WATER 24.71 mL/100 mL

Active Ingredient(s)

Alcohol 69.62% v/v

Purpose

Antiseptic

Use(s)

Hand sanitizer to help reduce bacteria that potentially can cause disease. For use when soap and water are not available.

Warnings

For external use only. Flamable. Keep away from heat or flame.

Do not use

- On children less than 2 months of age
- On open skin wounds

When using this product

keep out of eyes, ears and mouth. In case of contact with eyes, rinse eyes thoroughly with water.

Stop use and ask a doctor

if irritation occurs. These may be signs of a serious condition.

Keep out of reach of children.

If swallowed, get medical help or contact a Poison Control Center right away.

Directions

- Place enough product on hands to cover all surfaces. Rub hands together until dry.
- Supervise children under 6 years of age when using this product to avoid swallowing.

Other Information

- Store between 15-30C (59-86F)
- Avoid freezing and excessive heat above 40C (104F)

Inactive Ingredients:

Glycerine, Purified Water, Acrylate Copolymer, Aminomethyl Propanol, Fragrance.

Package Label - Principal Display Panel

3785 mL NDC: 75508-004-03

Package Label - Principal Display Panel

1892.7 mL NDC: 75508-004-10

Package Label - Principal Display Panel

946.35 mL NDC: 75508-004-04

Package Label - Principal Display Panel

473.17 mL NDC: 75508-004-05

Package Label - Principal Display Panel

236.58 mL NDC: 75508-004-06

Package Label - Principal Display Panel

177.44 mL NDC: 75508-004-07

Package Label - Principal Display Panel

118.3 mL NDC: 75508-004-08

Package Label - Principal Display Panel

59 mL NDC: 75508-004-09

Package Label - Principal Display Panel

208198 mL NDC: 75508-004-02

Package Label - Principal Display Panel

999349 mL NDC: 75508-004-01